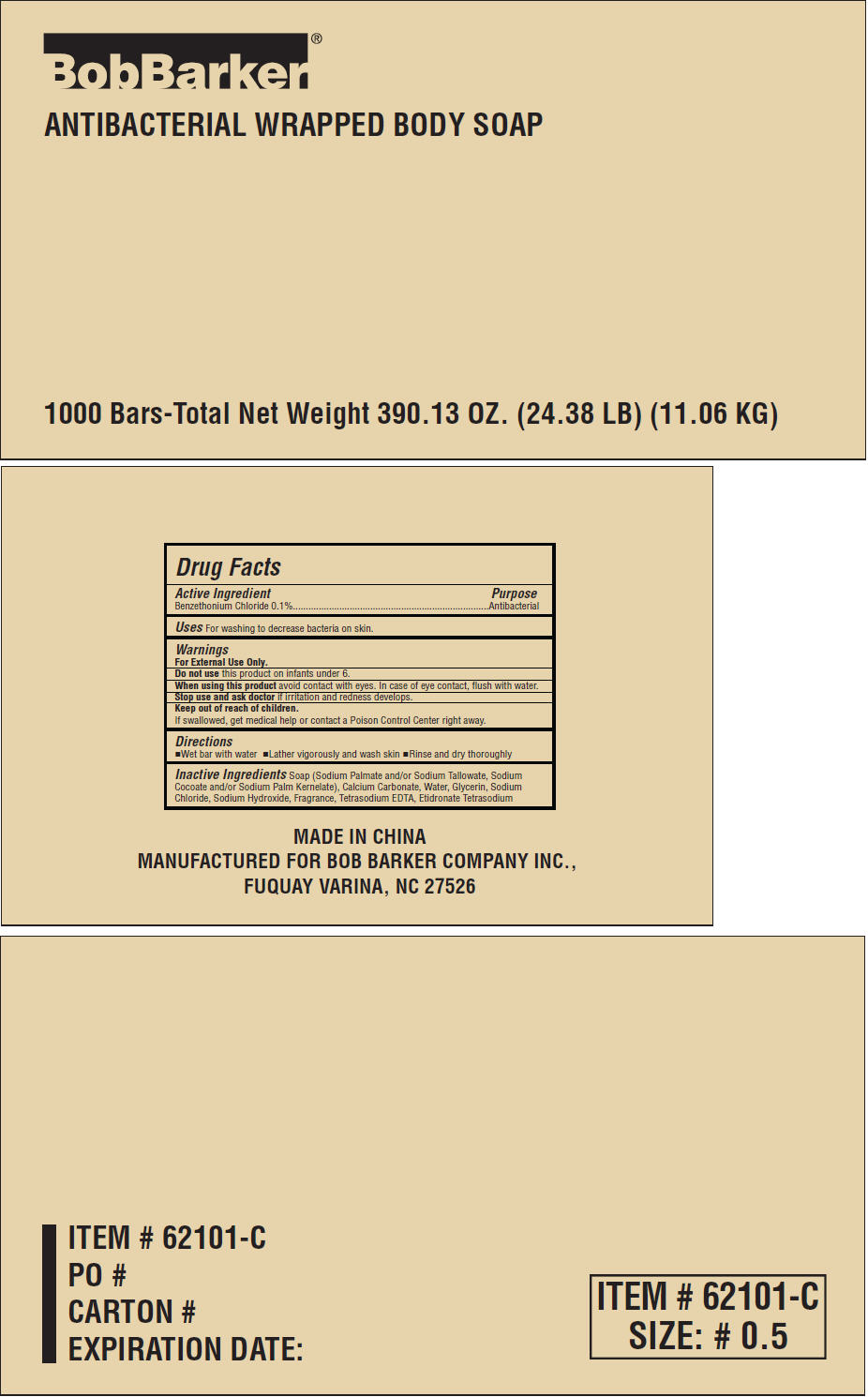 DRUG LABEL: Bob Barker Antibacterial wrapped body
NDC: 53247-107 | Form: SOAP
Manufacturer: Bob Barker Company Inc.
Category: otc | Type: HUMAN OTC DRUG LABEL
Date: 20190520

ACTIVE INGREDIENTS: BENZETHONIUM CHLORIDE 0.1 g/100 g
INACTIVE INGREDIENTS: Sodium Palmate; SODIUM TALLOWATE, BEEF; Sodium Cocoate; Sodium Palm Kernelate; Calcium Carbonate; Water; Glycerin; Sodium Chloride; Sodium Hydroxide; EDETATE SODIUM; Etidronate Tetrasodium

Bob Barker® Antibacterial wrapped body soap

Drug Facts

Active Ingredient

Benzethonium Chloride 0.1%

Purpose

Antibacterial

Uses

For washing to decrease bacteria on skin.

Warnings

For External Use Only.

Do not use this product on infants under 6.

When using this product avoid contact with eyes. In case of eye contact, flush with water.

Stop use and ask doctor if irritation and redness develops.

Keep out of reach of children.

If swallowed, get medical help or contact a Poison Control Center right away.

Directions

- Wet bar with water
- Lather vigorously and wash skin
- Rinse and dry thoroughly

Inactive Ingredients

Soap (Sodium Palmate and/or Sodium Tallowate, Sodium Cocoate and/or Sodium Palm Kernelate), Calcium Carbonate, Water, Glycerin, Sodium Chloride, Sodium Hydroxide, Fragrance, Tetrasodium EDTA, Etidronate Tetrasodium

PRINCIPAL DISPLAY PANEL - 1000 Bars Case

BobBarker®

ANTIBACTERIAL WRAPPED BODY SOAP

1000 Bars-Total Net Weight 390.13 OZ. (24.38 LB) (11.06 KG)